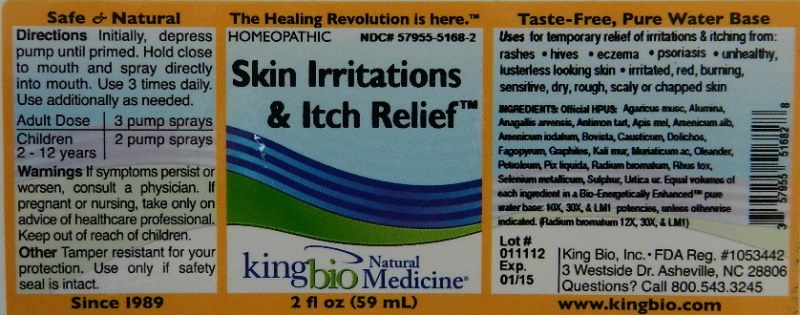 DRUG LABEL: Skin Irritations and Itch Relief
NDC: 57955-5168 | Form: LIQUID
Manufacturer: King Bio Inc.
Category: homeopathic | Type: HUMAN OTC DRUG LABEL
Date: 20120112

ACTIVE INGREDIENTS: AMANITA MUSCARIA VAR. MUSCARIA FRUITING BODY 10 [hp_X]/59 mL; ALUMINUM OXIDE 10 [hp_X]/59 mL; ANAGALLIS ARVENSIS 10 [hp_X]/59 mL; ANTIMONY POTASSIUM TARTRATE 10 [hp_X]/59 mL; APIS MELLIFERA 10 [hp_X]/59 mL; ARSENIC TRIOXIDE 10 [hp_X]/59 mL; ARSENIC TRIIODIDE 10 [hp_X]/59 mL; GIANT PUFFBALL 10 [hp_X]/59 mL; CAUSTICUM 10 [hp_X]/59 mL; MUCUNA PRURIENS FRUIT TRICHOME 10 [hp_X]/59 mL; FAGOPYRUM ESCULENTUM 10 [hp_X]/59 mL; GRAPHITE 10 [hp_X]/59 mL; POTASSIUM CHLORIDE 10 [hp_X]/59 mL; HYDROCHLORIC ACID 10 [hp_X]/59 mL; NERIUM OLEANDER LEAF 10 [hp_X]/59 mL; KEROSENE 10 [hp_X]/59 mL; PINE TAR 10 [hp_X]/59 mL; RADIUM BROMIDE 12 [hp_X]/59 mL; TOXICODENDRON PUBESCENS LEAF 10 [hp_X]/59 mL; SELENIUM 10 [hp_X]/59 mL; SULFUR 10 [hp_X]/59 mL; URTICA URENS 10 [hp_X]/59 mL
INACTIVE INGREDIENTS: WATER

Skin Irritations and Itch Relief

Active Ingredients

Official HPUS: Agaricus muscarius, Alumina, Anagallis arvensis, Antimonium tartaricum, Apis mellifica, Arsenicum album, Arsenicum Iodatum, Bovista, Causticum, Dolichos pruriens, Fagopyrum esculentum, Graphites, Kale muriaticum, Muriaticum acidum, Oleander Petroleum, Pix liquida, Radium bromatum, Rhus toxicodendron, Selenium metallicum, Sulphur and Urtica urens. Potencies at 10X, 30X and LM1 unless otherwise indicated.(Radium bromatum at 12X, 30X and LM1)

Reference image skin irritations.jpg

Inactive Ingredient

Equal volumes of each ingredient in a Bio-Energetically Enhanced Pure water base.

Reference image skin irritations.jpg

Dosage and Administration

Directions Initially, depress pump until primed. Hold close to mouth and spray one dose directly into mouth. Use 3 times daily. Use additionally as needed.

Adult Dose 3 pump sprays

Children 2-12 years 2 pump sprays

Reference image skin irritations.jpg

Purpose

Uses for temporary relief of irritations and itching from:

- rashes
- hives
- eczema
- psoriasis
- unhealthy, lusterless looking skin
- irritated, red burning, sensitive, dry rough, or chapped skin

Reference image skin irritations.jpg

Warnings

If symptoms persist or worsen, or if pregnant or nursing, take only on advice of a healthcare professional.

Other Information: Tamper resistant for your protection. Use only if safety seal is intact.

Reference image skin irritations.jpg

Keep out of reach of children.

Reference image skin irritations.jpg

Indications and Usage

Uses for temporary relief of irritations and itching from: rashes, hives, eczema, psoriasis, unhealthy, lusterless looking skin, irritated, red burning, sensitive, dry rough, or chapped skin

Reference image skin irritations.jpg

PACKAGE LABEL

King Bio Inc.

3 Westside Drive

Asheville, NC 28806

Questions? Call 800.543.3245

www.kingbio.com

Safe and Natural Homeopathic